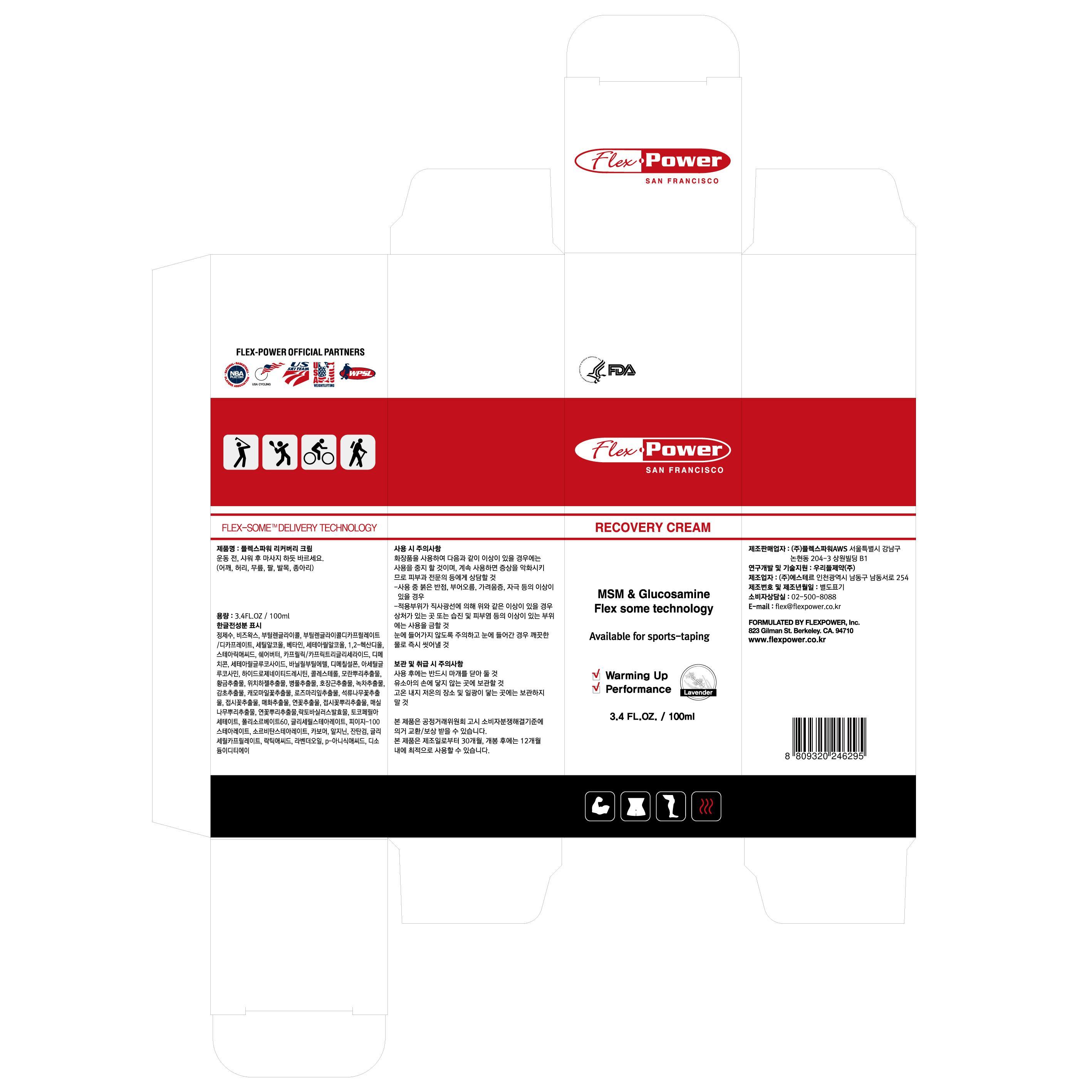 DRUG LABEL: Flex-Power Recovery
NDC: 70042-5001 | Form: CREAM
Manufacturer: Powerful X
Category: otc | Type: HUMAN OTC DRUG LABEL
Date: 20180829

ACTIVE INGREDIENTS: DIMETHICONE 1 g/100 mL
INACTIVE INGREDIENTS: WATER; BUTYLENE GLYCOL

Drug Facts

ACTIVE INGREDIENT

dimethicone

INACTIVE INGREDIENT

Water, Beeswax, Butylene Glycol, Butylene Glycol Dicaprylate/Dicaprate, Cetyl Alcohol, Cetearyl Alcohol, Betaine, 1,2-Hexanedioln, Stearic Acid, Butyrospermum Parkii (Shea) Butter, Caprylic/Capric Triglyceride, Polysorbate60, Sorbitan Stearate,Vanillyl Butyl Ether, Arginine, PEG-100 Stearate, Portulaca Oleracea Extract, Xanthan Gum, Glyceryl Stearate, Cetearyl Glucoside, p-Anisic Acid, Glyceryl Caprylate, Tocopheryl Acetate, Acetyl Glucosamine, Dimethyl Sulfone, Carbomer, Lavandula Angustifolia (Lavender) Oil, Centella Asiatica Extract, Cucurbita Pepo (Pumpkin) Fruit Extract, Opuntia Ficus-Indica Stem Extract, Hydrogenated Lecithin, Disodium EDTA, Polygonum Cuspidatum Root Extract, Scutellaria Baicalensis Root Extract, Camellia Sinensis Leaf Extract, Glycyrrhiza Glabra (Licorice) Root Extract, Lactic Acid, Chamomilla Recutita (Matricaria) Flower Extract, Rosmarinus Officinalis (Rosemary) Leaf Extract, Cholesterol, Punica Granatum Flower Extract, Althaea Rosea Flower Extract, Prunus Mume Flower Extract, Nelumbo Nucifera Flower Extract, Althaea Rosea Root Extract, Prunus Mume Root Extract, Nelumbo Nucifera Root Extract, Lactobacillus Ferment

PURPOSE

skin protectant

keep out of reach of the children

INDICATIONS AND USAGE

apply proper amount to the skin

WARNINGS

1. Do not use in the following cases(Eczema and scalp wounds)
2.Side Effects
1)Due to the use of this druf if rash, irritation, itching and symptopms of hypersnesitivity occur dicontinue use and consult your phamacisr or doctor
3.General Precautions
1)If in contact with the eyes, wash out thoroughty with water If the symptoms are servere, seek medical advice immediately
2)This product is for exeternal use only. Do not use for internal use
4.Storage and handling precautions
1)If possible, avoid direct sunlight and store in cool and area of low humidity
2)In order to maintain the quality of the product and avoid misuse
3)Avoid placing the product near fire and store out in reach of children

DOSAGE AND ADMINISTRATION

for external use only